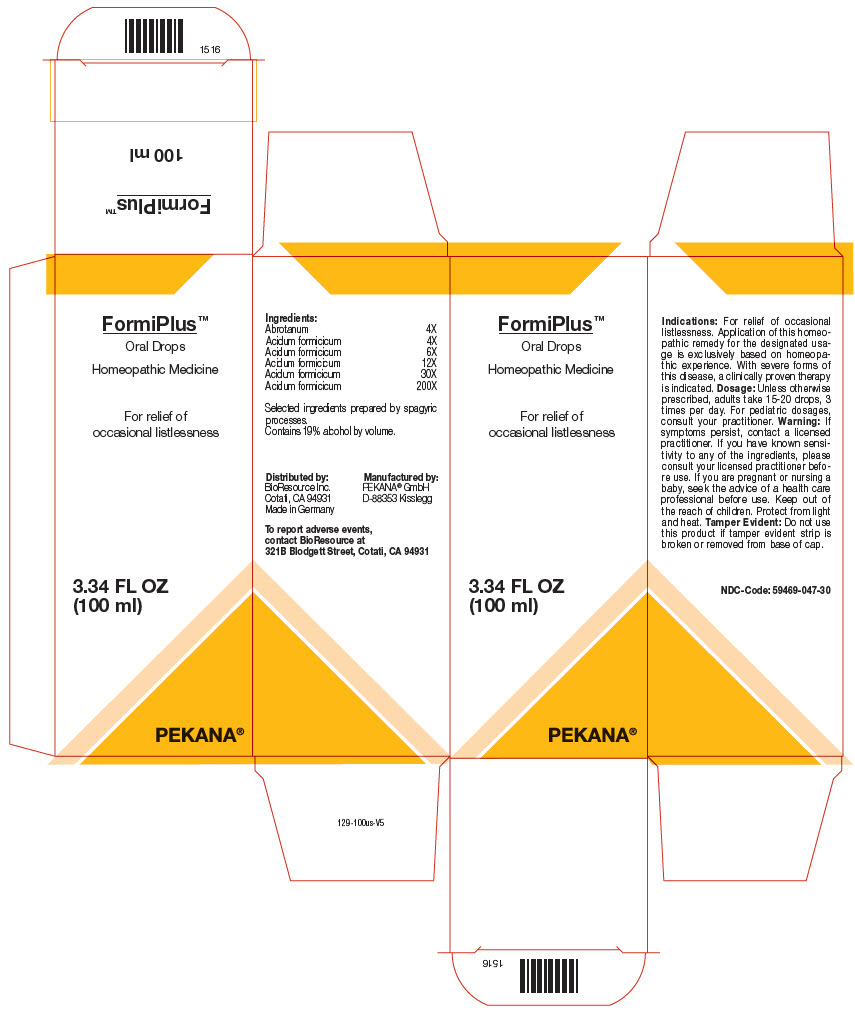 DRUG LABEL: FORMIPLUS
NDC: 59469-047 | Form: SOLUTION/ DROPS
Manufacturer: PEKANA Naturheilmittel GmbH
Category: homeopathic | Type: HUMAN OTC DRUG LABEL
Date: 20221222

ACTIVE INGREDIENTS: Artemisia abrotanum Flowering Top 4 [hp_X]/100 mL; Formic Acid 200 [hp_X]/100 mL
INACTIVE INGREDIENTS: Water; Alcohol

FORMIPLUS™

ACTIVE INGREDIENT

Ingredients:
Abrotanum | 4X
Acidum formicicum | 4X
Acidum formicicum | 6X
Acidum formicicum | 12X
Acidum formicicum | 30X
Acidum formicicum | 200X

Selected ingredients prepared by spagyric processes.

INACTIVE INGREDIENT

Contains 19% alcohol by volume.

Indications

PURPOSE

For relief of occasional listlessness. Application of this homeopathic remedy for the designated usage is exclusively based on homeopathic experience. With severe forms of this disease, a clinically proven therapy is indicated.

Dosage

Unless otherwise prescribed, adults take 15-20 drops, 3 times per day. For pediatric dosages, consult your practitioner.

Warning

ASK DOCTOR

If symptoms persist, contact a licensed practitioner. If you have known sensitivity to any of the ingredients, please consult your licensed practitioner before use. If you are pregnant or nursing a baby, seek the advice of a health care professional before use.

Keep out of the reach of children.

STORAGE AND HANDLING

Protect from light and heat.

Tamper Evident

Do not use this product if tamper evident strip is broken or removed from base of cap.

QUESTIONS

To report adverse events, contact BioResource at 321B Blodgett Street, Cotati, CA 94931

Distributed by:
BioResource Inc.
Cotati, CA 94931

Manufactured by:
PEKANA® GmbH
D-88353 Kisslegg

PRINCIPAL DISPLAY PANEL - 100 ml Bottle Box

FormiPlus™
Oral Drops

Homeopathic Medicine

For relief of
occasional listlessness

3.34 FL OZ
(100 ml)

PEKANA®